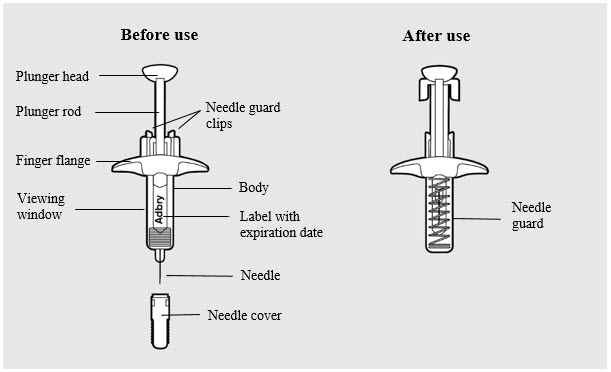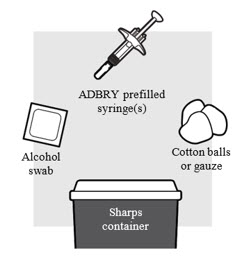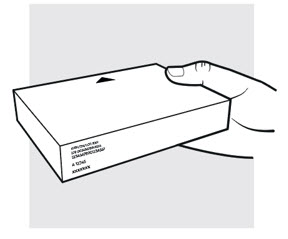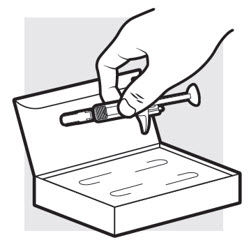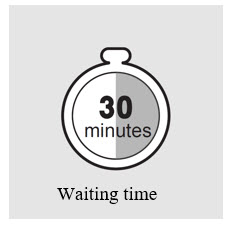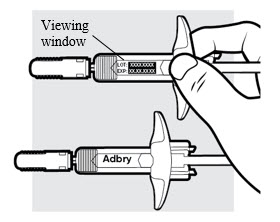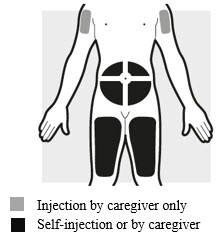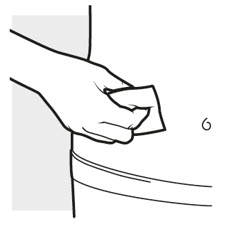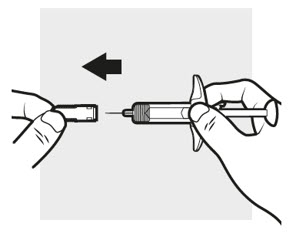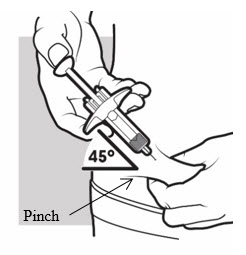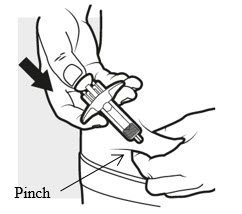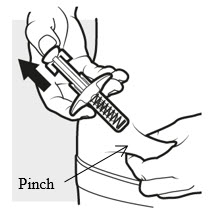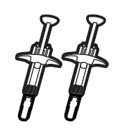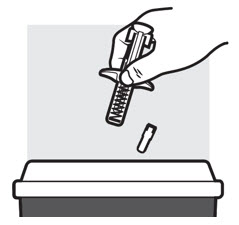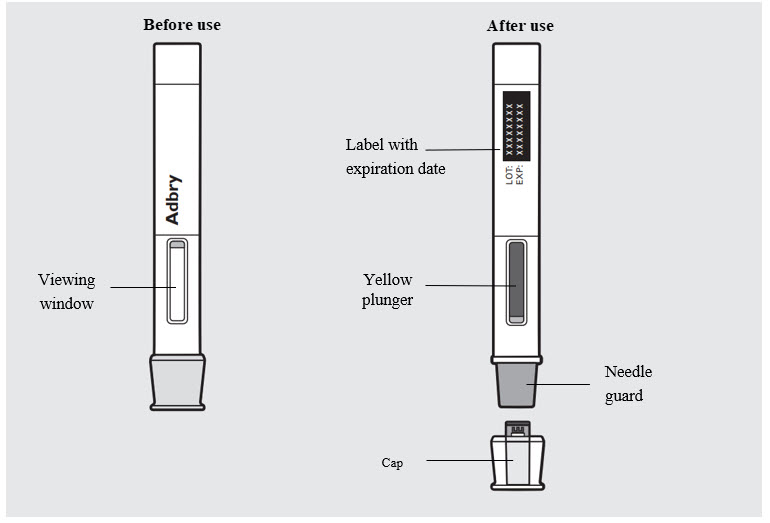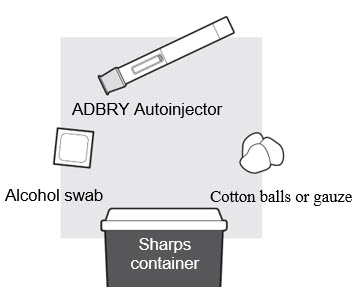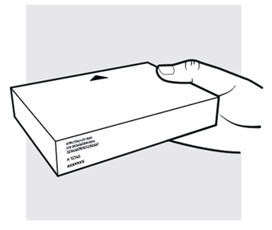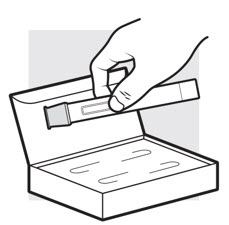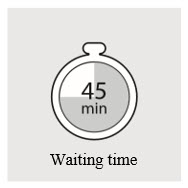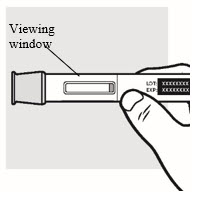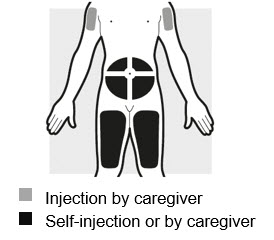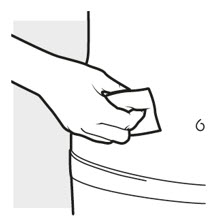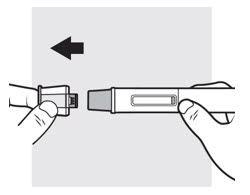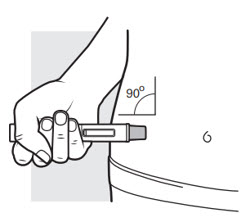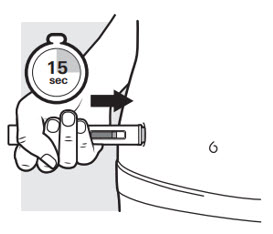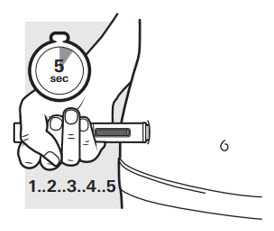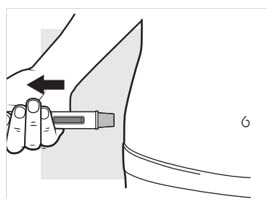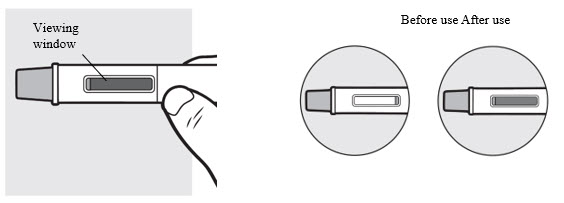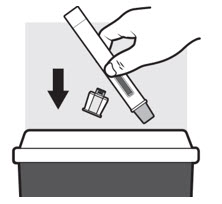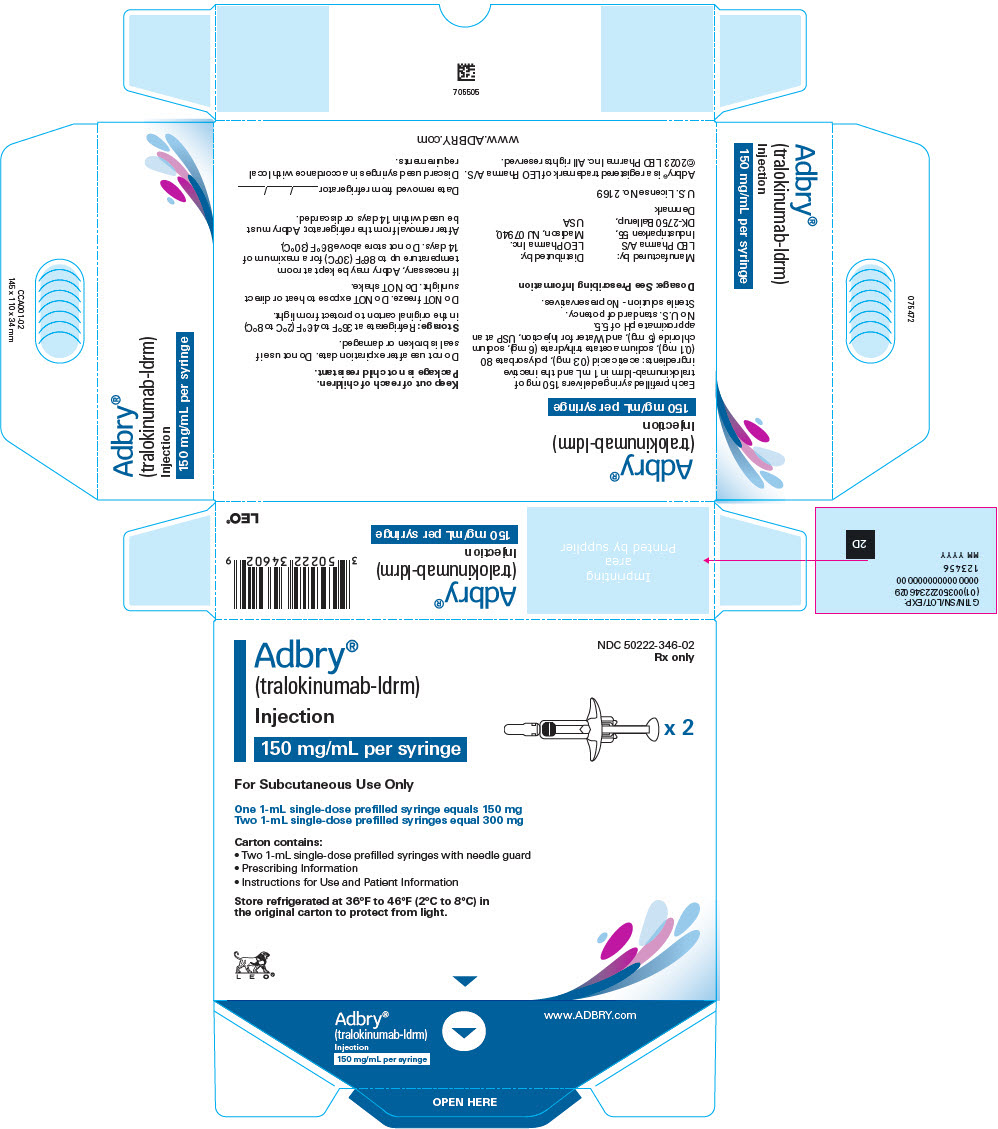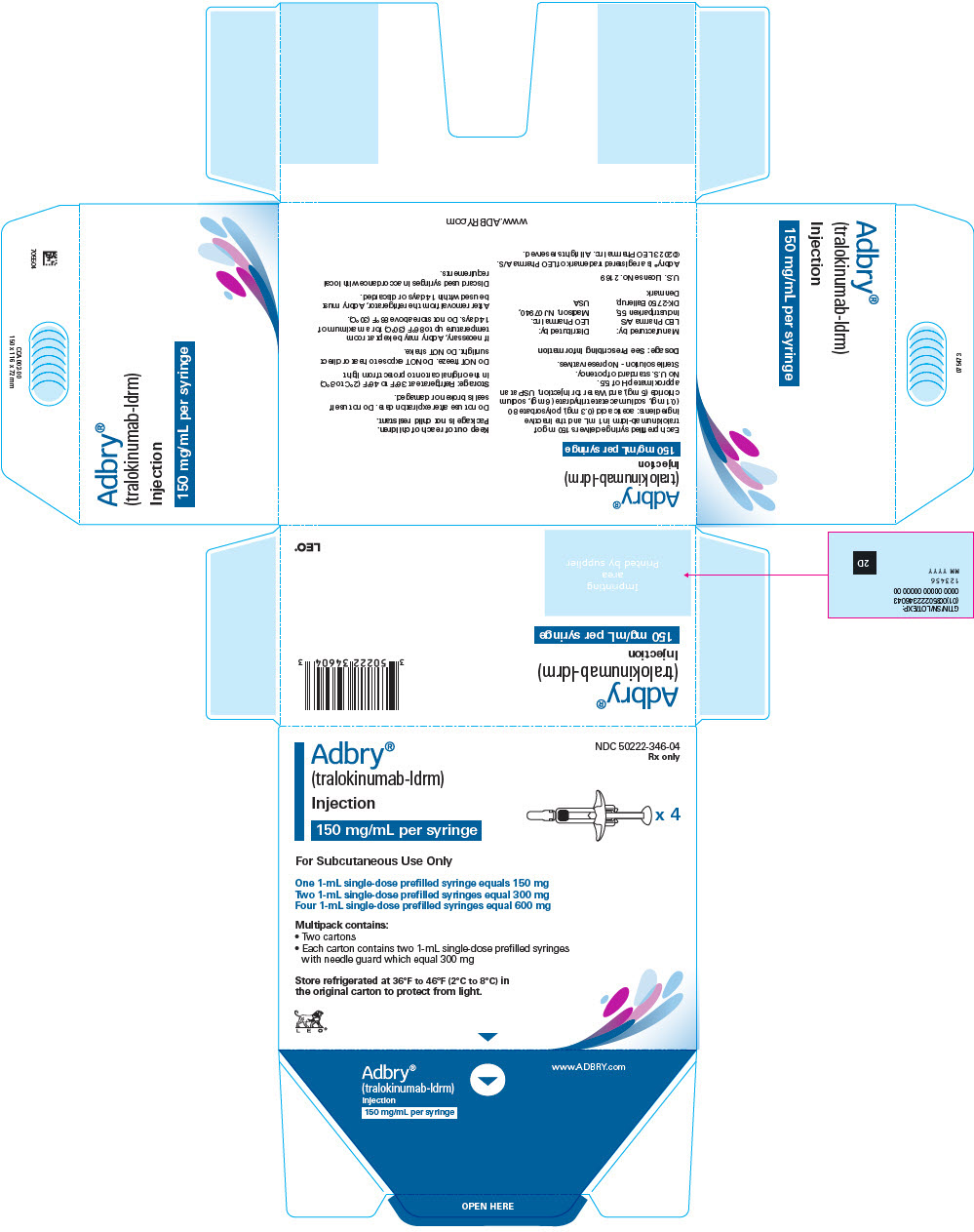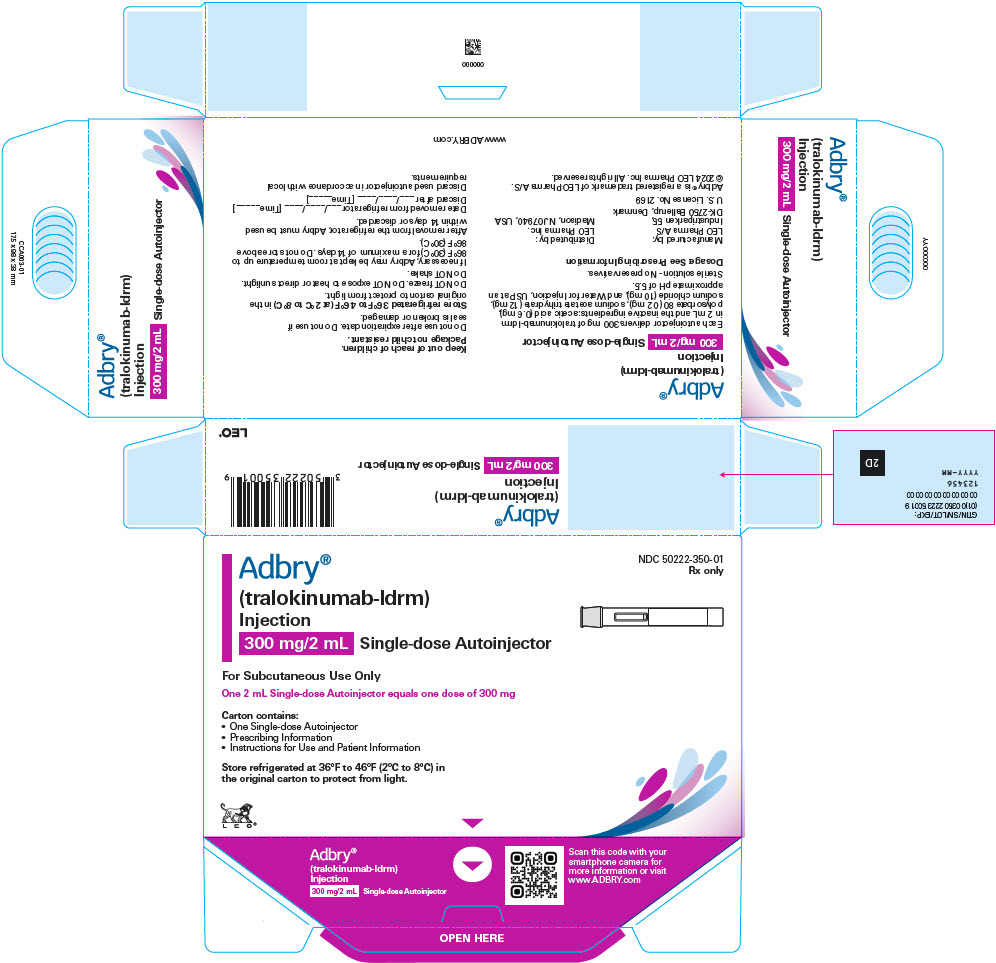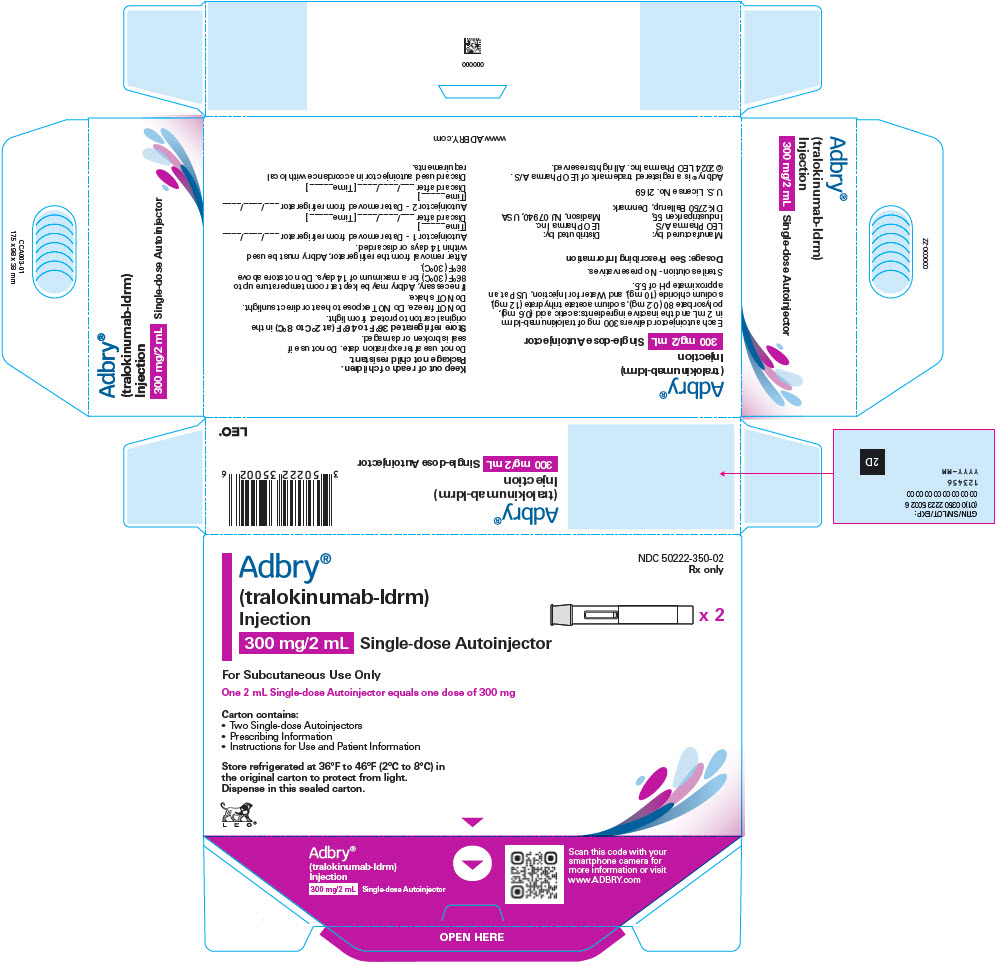 DRUG LABEL: Adbry
NDC: 50222-346 | Form: INJECTION, SOLUTION
Manufacturer: LEO Pharma Inc.
Category: prescription | Type: HUMAN PRESCRIPTION DRUG LABEL
Date: 20251217

ACTIVE INGREDIENTS: TRALOKINUMAB 150 mg/1 mL
INACTIVE INGREDIENTS: ACETIC ACID 0.3 mg/1 mL; POLYSORBATE 80 0.1 mg/1 mL; SODIUM ACETATE 6 mg/1 mL; SODIUM CHLORIDE 5 mg/1 mL; WATER

HIGHLIGHTS OF PRESCRIBING INFORMATION

These highlights do not include all the information needed to use ADBRY safely and effectively. See full prescribing information for ADBRY.
ADBRY® (tralokinumab-ldrm) injection, for subcutaneous use
Initial U.S. Approval: 2021

1 INDICATIONS AND USAGE

ADBRY is an interleukin-13 antagonist indicated for the treatment of moderate-to-severe atopic dermatitis in adults and pediatric patients 12 years of age and older whose disease is not adequately controlled with topical prescription therapies or when those therapies are not advisable. ADBRY can be used with or without topical corticosteroids. (1)

2 DOSAGE AND ADMINISTRATION

- Prior to ADBRY initiation, complete all age appropriate vaccinations as recommended by current immunization guidelines (2.1)
- Administer ADBRY by subcutaneous injection. (2.2)
- In pediatric patients 12 years of age and older, it is recommended that ADBRY be given by or under supervision of an adult. (2.2)
- The recommended dosage of ADBRY (2.3)

Dosage in Adults

 | Initial Loading Dose | Subsequent Dosage
Prefilled syringe | 600 mg (four 150 mg injections) | 300 mg (two 150 mg injections) every other week
Autoinjector | 600 mg (two 300 mg injections) | 300 mg (one 300 mg injection) every other week

Dosage in Pediatric Patients 12 Years of Age and Older

 | Initial Loading Dose | Subsequent Dosage
Prefilled syringe | 300 mg (two 150 mg injections) | 150 mg (one 150 mg injection) every other week

- A dosage of 300 mg every 4 weeks may be considered for adult patients below 100 kg who achieve clear or almost clear skin after 16 weeks of treatment. (2.3)

3 DOSAGE FORMS AND STRENGTHS

Injection:

- 150 mg/mL solution in a single-dose prefilled syringe with needle guard. (3)
- 300 mg/2 mL solution in a single-dose autoinjector (3)

4 CONTRAINDICATIONS

Known hypersensitivity to tralokinumab-ldrm or any excipients in ADBRY. (4)

5 WARNINGS AND PRECAUTIONS

- Hypersensitivity: Hypersensitivity reactions, including anaphylaxis, and angioedema have occurred after administration of ADBRY. Discontinue ADBRY in the event of a hypersensitivity reaction. (5.1)
- Conjunctivitis and Keratitis: Patients should report new onset or worsening eye symptoms to their healthcare provider. (5.2)
- Parasitic (Helminth) Infections: Treat patients with pre-existing helminth infections before initiating treatment with ADBRY. If patients become infected while receiving ADBRY and do not respond to anti-helminth treatment, discontinue treatment with ADBRY until the infection resolves. (5.3)
- Risk of Infection with Live Vaccines: Avoid use of live vaccines. (5.4)

6 ADVERSE REACTIONS

Most common adverse reactions (incidence ≥ 1%) are upper respiratory tract infections, conjunctivitis, injection site reactions, and eosinophilia. (6.1)

To report SUSPECTED ADVERSE REACTIONS, contact LEO Pharma Inc. at 1-877-494-4536 or FDA at 1-800-FDA-1088 or www.fda.gov/medwatch.

FULL PRESCRIBING INFORMATION

1 INDICATIONS AND USAGE

ADBRY is indicated for the treatment of moderate-to-severe atopic dermatitis in adults and pediatric patients 12 years of age and older whose disease is not adequately controlled with topical prescription therapies or when those therapies are not advisable. ADBRY can be used with or without topical corticosteroids.

2 DOSAGE AND ADMINISTRATION

2.1 Vaccination Prior to Treatment

Complete all age-appropriate vaccinations as recommended by current immunization guidelines prior to initiating treatment with ADBRY [see Warnings and Precautions (5.4)].

2.2 Important Administration Instructions

- ADBRY is administered by subcutaneous injection.
- ADBRY is intended for use under the guidance of a healthcare provider. Provide proper training to patients and/or caregivers on the preparation and administration of ADBRY prior to use according to the "Instructions for Use" [see Instructions for Use].

Use of the Autoinjector

- The ADBRY autoinjector is for use in adults only.
- A caregiver or adult patient may inject ADBRY using the autoinjector.

Use of the Prefilled Syringe

- The ADBRY prefilled syringe is for use in adults and pediatric patients 12 years of age and older.
- A caregiver or patient 12 years of age and older may inject ADBRY using the prefilled syringe. In pediatric patients 12 years of age and older, administer ADBRY under the supervision of an adult.

Administration Instructions

- Administer subcutaneous injection into the thigh or abdomen, except for the 2 inches (5 cm) around the navel. The upper arm can also be used if a caregiver administers the injection.
- DO NOT inject ADBRY into skin that is tender, damaged, bruised, or scarred.
- For adults taking the initial loading dose of 600 mg, administer each of the injections (four ADBRY 150 mg injections using prefilled syringes or two ADBRY 300 mg injections using autoinjectors) at different injection sites within the same body area.
  - For the subsequent 300 mg doses using the prefilled syringe, administer the two ADBRY 150 mg injections at different injection sites within the same body area, rotating the body area with each subsequent set of injections.
  - For the subsequent 300 mg doses using the autoinjector, administer one ADBRY 300 mg injection, rotating the body area with each subsequent injection
- For pediatric patients 12 years of age and older taking the initial loading dose of 300 mg, use prefilled syringes to administer the two ADBRY 150 mg injections at different injection sites within the same body area.
  - For the subsequent 150 mg doses, use a prefilled syringe to administer one ADBRY 150 mg injection, rotating the body area with each subsequent injection.
- The ADBRY "Instructions for Use" contains more detailed instructions on the preparation and administration of ADBRY [see Instructions for Use].

2.3 Recommended Dosage

Dosage in Adults

The recommended dosage for adults is:

 | Initial Loading Dose | Subsequent Dosage
Prefilled syringe | 600 mg (four 150 mg injections) | 300 mg (two 150 mg injections) every other week
Autoinjector | 600 mg (two 300 mg injections) | 300 mg (one 300 mg injection) every other week

After 16 weeks of treatment, for adult patients with body weight below 100 kg who achieve clear or almost clear skin, a dosage of 300 mg every 4 weeks may be considered.

Dosage in Pediatric Patients 12 Years of Age and Older

The recommended dosage for pediatric patients 12 years of age and older is:

 | Initial Loading Dose | Subsequent Dosage
Prefilled syringe | 300 mg (two 150 mg injections) | 150 mg (one 150 mg injection) every other week

2.4 Concomitant Topical Therapies

ADBRY can be used with or without topical corticosteroids. Topical calcineurin inhibitors may be used, but should be reserved for problem areas only, such as the face, neck, intertriginous and genital areas.

2.5 Missed Doses

If a dose is missed, administer the dose as soon as possible. Thereafter, resume dosing at the regular scheduled time.

2.6 Preparation for Use

- Before injection, remove ADBRY prefilled syringes or autoinjectors from the refrigerator and allow to reach room temperature (at least 30 minutes for the prefilled syringes and at least 45 minutes for the autoinjectors) without removing the needle cover or cap, respectively.
- After removal from the refrigerator, ADBRY may be kept at room temperature up to 30°C (86°F) and must be used within 14 days or discarded.
- Inspect ADBRY visually for particulate matter and discoloration prior to administration. ADBRY injection is a clear to opalescent, colorless to pale yellow solution. Do not use if the liquid contains visible particulate matter, is discolored or cloudy (other than clear to opalescent, colorless to pale yellow).
- ADBRY does not contain preservatives; therefore, discard any unused product.

3 DOSAGE FORMS AND STRENGTHS

ADBRY is a clear to opalescent, colorless to pale yellow solution available as:

- Injection: 150 mg/mL solution in a single-dose prefilled syringe with needle guard
- Injection: 300 mg/2 mL solution in a single-dose autoinjector

4 CONTRAINDICATIONS

ADBRY is contraindicated in patients who have known hypersensitivity to tralokinumab-ldrm or any excipients in ADBRY [see Warnings and Precautions (5.1)].

5 WARNINGS AND PRECAUTIONS

5.1 Hypersensitivity

Hypersensitivity reactions including anaphylaxis and angioedema have been reported with use of ADBRY.

If a serious hypersensitivity reaction occurs, discontinue ADBRY immediately and initiate appropriate therapy.

5.2 Conjunctivitis and Keratitis

Conjunctivitis and keratitis occurred more frequently in atopic dermatitis subjects who received ADBRY. Conjunctivitis was the most frequently reported eye disorder. Most subjects with conjunctivitis or keratitis recovered or were recovering during the treatment period [see Adverse Reactions (6.1)].

Advise patients to report new onset or worsening eye symptoms to their healthcare provider.

5.3 Parasitic (Helminth) Infections

Patients with known helminth infections were excluded from participation in clinical studies. It is unknown if ADBRY will influence the immune response against helminth infections by inhibiting IL-13 signaling.

Treat patients with pre-existing helminth infections before initiating treatment with ADBRY. If patients become infected while receiving ADBRY and do not respond to antihelminth treatment, discontinue treatment with ADBRY until the infection resolves.

5.4 Risk of Infection with Live Vaccines

ADBRY may alter a patient's immunity and increase the risk of infection following administration of live vaccines. Prior to initiating therapy with ADBRY, complete all age-appropriate vaccinations according to current immunization guidelines. Avoid use of live vaccines during treatment with ADBRY. Limited data are available regarding coadministration of ADBRY with non-live vaccines [see Clinical Pharmacology (12.2)].

6 ADVERSE REACTIONS

The following adverse reactions are discussed in greater detail elsewhere in the labeling:

- Hypersensitivity [see Warnings and Precautions (5.1)]
- Conjunctivitis and Keratitis [see Warnings and Precautions (5.2)]

6.1 Clinical Trials Experience

Because clinical trials are conducted under widely varying conditions, adverse reaction rates observed in the clinical trials of a drug cannot be directly compared to rates in the clinical trials of another drug and may not reflect the rates observed in practice.

Adverse Reactions from Clinical Trials in Adults

The safety of ADBRY was evaluated in a pool of 5 randomized, double-blind, placebo-controlled trials in subjects with moderate-to-severe atopic dermatitis including three phase 3 Eczema Tralokinumab trials (ECZTRA 1, ECZTRA 2, and ECZTRA 3), a dose-finding trial, and a vaccine response trial. The safety population had a mean age of 37 years; 43% of subjects were female, 67% were White, 21% were Asian, and 9% were Black. In terms of co-morbid conditions, 39% of the subjects had asthma, 49% had hay fever, 36% had food allergy, and 21% had allergic conjunctivitis at baseline.

In these 5 atopic dermatitis trials, 1964 subjects were treated with subcutaneous injections of ADBRY, with or without concomitant topical corticosteroids (TCS). A total of 807 subjects were treated with ADBRY for at least 1 year.

ECZTRA 1 and ECZTRA 2 compared the safety of ADBRY monotherapy to placebo through Week 52. ECZTRA 3 compared the safety of ADBRY + TCS to placebo + TCS through Week 32.

Weeks 0 to 16 (ECZTRA 1, ECZTRA 2, and ECZTRA 3):

Table 1 summarizes the adverse reactions identified in the pool of 3 trials (ECZTRA 1, ECZTRA 2, and ECZTRA 3) and that occurred at a rate of at least 1% in the ADBRY 300 mg every other week monotherapy group, and in the ADBRY 300 mg every other week + TCS trial, all at a higher rate than placebo during the first 16 weeks of treatment.

Table 1: Adverse Reactions Occurring in ≥1% of the ADBRY Monotherapy Group or the ADBRY + TCS Group in the Atopic Dermatitis Trials through Week 16
Adverse Reaction | ADBRY Monotherapy [Pooled analysis of ECZTRA 1 and ECZTRA 2.] |  | ADBRY + TCS [Analysis of ECZTRA 3 where subjects were on background TCS therapy.]
Adverse Reaction | ADBRY 300 mg Q2W [ADBRY 600 mg at Week 0, followed by 300 mg every other week.] | PLACEBO | ADBRY 300 mg Q2W + TCS | PLACEBO + TCS
 | N=1180 n (%) | N=388 n (%) | N=243 n (%) | N=123 n (%)
Upper respiratory tract infections [Upper respiratory tract infections cluster includes upper respiratory tract infection, viral upper respiratory tract infection, pharyngitis, and nasopharyngitis; mainly reported as common cold.] | 281 (23.8) | 79 (20.4) | 73 (30.0) | 19 (15.4)
Conjunctivitis [Conjunctivitis cluster includes conjunctivitis and allergic conjunctivitis.] | 88 (7.5) | 12 (3.1) | 33 (13.6) | 6 (4.9)
Injection site reactions [Injection site reactions cluster includes pain, erythema, and swelling.] | 87 (7.4) | 16 (4.1) | 27 (11.1) | 1 (0.8)
Eosinophilia [Eosinophilia cluster includes eosinophilia and eosinophil count increased.] | 17 (1.4) | 2 (0.5) | 3 (1.2) | 0

In the monotherapy trials (ECZTRA 1 and ECZTRA 2) through Week 16, the proportion of subjects who discontinued treatment due to adverse reactions was 0.7% in the ADBRY 300 mg every other week group and 0% of the placebo group. In the concomitant TCS trial (ECZTRA 3) through Week 16, the proportion of subjects who discontinued treatment due to adverse reactions was 0.8% in the ADBRY 300 mg every other week +TCS group and 0% of the placebo + TCS group. The most common adverse reactions leading to discontinuation in the ADBRY group compared to the placebo group were injection site reaction (0.3% v. 0) and eosinophilia (0.3% v. 0) in ECZTRA 1 and ECZTRA 2; and injection site reaction (0.4% v. 0) and conjunctivitis (0.4% v. 0) in ECZTRA 3.

Weeks 16-52 (ECZTRA 1 and ECZTRA 2) and Weeks 16-32 (ECZTRA 3):

The safety profile of ADBRY 300 mg every other week with or without TCS during maintenance treatment was consistent with that in the initial 16-week treatment period. In addition, the frequency of adverse reactions with ADBRY 300 mg every other week and every 4 weeks in ECZTRA 1 and ECZTRA 2 was 44% and 34%, respectively, and 43% and 26% with ADBRY 300 mg + TCS every other week and every 4 weeks in ECZTRA 3, respectively.

Adverse Reactions from Clinical Trials in Pediatric Subjects 12 Years of Age and Older

The safety of tralokinumab was assessed in a trial of 289 subjects 12 to 17 years of age with moderate-to-severe atopic dermatitis (ECZTRA 6). Of the 289 subjects, 195 were treated with ADBRY and 94 were treated with matching placebo. The safety profile of ADBRY in these subjects, assessed through the initial treatment period of 16 weeks and the long-term period of 52 weeks, was comparable to the safety profile from trials in adults with atopic dermatitis.

Safety through 268 weeks (ECZTEND)

ECZTEND was an open-label, multicenter, long-term extension trial that further assessed the safety of ADBRY for up to 5 years of treatment in adults and pediatric subjects 12 years of age and older with moderate-to-severe atopic dermatitis who had previously participated in ADBRY trials. The safety data in ECZTEND reflect exposure to ADBRY in 1672 subjects who received 300 mg of ADBRY every two weeks (Q2W), including 1422 exposed for at least 52 weeks, 1184 exposed for at least 104 weeks, 701 exposed for at least 156 weeks, and 33 exposed for at least 264 weeks.

The long-term safety profile was consistent with the safety profile observed up to week 16.

Specific Adverse Reactions

Conjunctivitis and Keratitis

Conjunctivitis, including allergic conjunctivitis, was reported in 7.5% of subjects treated with ADBRY 300 mg every other week (29 events per 100 subject-years of exposure) and in 3.1% of subjects treated with placebo (12 events per 100 subject-years of exposure) in the initial treatment period of up to 16 weeks in the pool of 5 trials. In the ADBRY group, 126 subjects reported 145 events of conjunctivitis, with 114 events resolved at the end of initial treatment period. Conjunctivitis led to discontinuation of treatment in 2 subjects.

During the initial treatment period of the monotherapy trials (ECZTRA 1 and ECZTRA 2), conjunctivitis was reported in 7.7% of subjects treated with ADBRY 300 mg every other week (30 events per 100 subject-years of exposure).

During the maintenance treatment period of the monotherapy trials (ECZTRA 1 and ECZTRA 2) from 16 to 52 weeks, conjunctivitis was reported in 14 (8.9%) subjects treated with ADBRY 300 mg every other week (20 events per 100 subject-years of exposure) and in 10 (6.3%) subjects treated with ADBRY 300 mg every 4 weeks (14 events per 100 subject-years of exposure); and included no serious events, 1 severe event, and 1 event that led to discontinuation. A comparable pattern was seen during the continuation treatment period of an additional 16 weeks in the ADBRY combination trial ECZTRA 3.

Keratoconjunctivitis (including 1 atopic keratoconjunctivitis (0.1%)) was reported in 5 (0.3%) subjects (1.2 events per 100 subject-years of exposure) treated with ADBRY and 0% of subjects treated with placebo during the initial treatment period of up to 16 weeks in the pool of 5 trials. Keratoconjunctivitis was reported as resolved in 2 out of 5 subjects by the end of trials.

Keratitis (including 1 ulcerative keratitis (0.1%)) was reported in 4 (0.2%) subjects treated with ADBRY (0.9 events per 100 subject-years of exposure) and 1 (0.2%) subject (viral keratitis) treated with placebo (0.6 events per 100 subject-years of exposure) during the initial treatment period of up to 16 weeks in the pool of 5 trials. Keratitis was reported as resolved in all but 1 subject by the end of trials. None of the events were serious or led to treatment discontinuation.

During the initial treatment period of the monotherapy trials (ECZTRA 1 and ECZTRA 2), keratitis event rate of 2 per 100 subject-years was reported for ADBRY 300 mg every other week.

During the maintenance treatment period of the monotherapy trials (ECZTRA 1 and ECZTRA 2) from 16 to 52 weeks in the ADBRY 300 mg every other week group, keratitis was reported in 1 (0.6%) subject (ulcerative, severe, resolved after discontinuation) at an exposure-adjusted event rate of 1.2 per 100 subject-years, and keratoconjunctivitis (not serious or severe, resolved, not led to discontinuation) was reported in 3 (1.9%) subjects (3.6 events per 100 subject-years of exposure). No events of keratitis or keratoconjunctivitis was reported in ADBRY every 4 weeks or placebo groups. In the continuation treatment period of ECZTRA 3 (from 16 to 32 weeks), there were no additional events of keratitis reported for subjects randomized to ADBRY 300 mg + TCS.

Eosinophil Counts

ADBRY-treated subjects had a greater mean initial increase from baseline in eosinophil count compared to subjects treated with placebo. The mean and median increases in blood eosinophils from baseline to Week 4 were 190 and 100 cells/mcL, respectively. The increase in the ADBRY-treated subjects declined to baseline level with continued treatment. Eosinophilia (> 5000 cells/mcL) in the initial treatment period of up to 16 weeks was reported in 1.2% in the ADBRY-treated subjects and 0.3% in the placebo-treated subjects. The safety profile for subjects with eosinophilia was comparable to the safety profile for all subjects included in the pool of 5 atopic dermatitis trials.

8 USE IN SPECIFIC POPULATIONS

8.1 Pregnancy

Pregnancy Exposure Registry

There is a pregnancy exposure registry that monitors pregnancy outcomes in women exposed to ADBRY during pregnancy. Healthcare providers are encouraged to register pregnant patients, or pregnant women may enroll themselves in the registry by calling 1-877-311-8972 or visiting https://mothertobaby.org/ongoing-study/adbry-tralokinumab/.

Risk Summary

There are limited data from the use of ADBRY in pregnant women to inform a drug-associated risk of adverse developmental outcomes. Monoclonal antibodies are actively transported across the placenta (see Clinical Considerations).

In an enhanced pre-and post-natal developmental study, no adverse developmental effects were observed in offspring born to pregnant monkeys after intravenous administration of tralokinumab-ldrm during organogenesis through parturition at doses up to 10 times the maximum recommended human dose (MRHD).

The background risk of major birth defects and miscarriage for the indicated population is unknown. All pregnancies have a background risk of birth defect, loss or other adverse outcomes. In the U.S. general population, the estimated background risk of major birth defects and miscarriage in clinically recognized pregnancies is 2% to 4% and 15% to 20%, respectively.

Clinical Considerations

Fetal/Neonatal Adverse Reactions

Transport of endogenous IgG antibodies across the placenta increases as pregnancy progresses and peaks during the third trimester. Therefore, ADBRY may be present in infants exposed in utero. The potential clinical impact of tralokinumab-ldrm exposure in infants exposed in utero should be considered.

Data

Animal Data

In a pre- and post-natal development study, intravenous doses up to 100 mg/kg tralokinumab-ldrm were administered to pregnant cynomolgus monkeys once every week from gestation day 20 to parturition. No maternal or developmental toxicity was observed at doses up to 100 mg/kg/week (10 times the MRHD on a mg/kg basis of 10 mg/kg/week).

In an enhanced pre- and post-natal development study, intravenous doses up to 100 mg/kg tralokinumab-ldrm (10 times the MRHD on a mg/kg basis of 10 mg/kg/week) were administered to pregnant cynomolgus monkeys once every week from the beginning of organogenesis to parturition. No treatment-related adverse effects on embryofetal toxicity or malformations, or on morphological, functional, or immunological development were observed in the infants from birth through 6 months of age.

8.2 Lactation

Risk Summary

There are no data on the presence of tralokinumab-ldrm in human milk, the effects on the breastfed infant, or the effects on milk production. Maternal IgG is present in breast milk. The effects of local gastrointestinal exposure and limited systemic exposure to ADBRY on the breastfed infant are unknown. The development and health benefits of breastfeeding should be considered along with the mother's clinical need for ADBRY and any potential adverse effects on the breastfed child from ADBRY or from the underlying maternal condition.

8.4 Pediatric Use

The safety and effectiveness of ADBRY have been established for the treatment of moderate-to-severe atopic dermatitis in pediatric patients 12 years of age and older whose disease is not adequately controlled with topical prescription therapies or when those therapies are not advisable.

Use of ADBRY in this age group is supported by a multicenter, randomized, double-blind, placebo-controlled trial (ECZTRA 6) in 289 subjects 12 to 17 years of age with moderate-to-severe atopic dermatitis. Of the 289 subjects, 195 were treated with ADBRY and 94 were treated with matching placebo. The safety and effectiveness were consistent between subjects 12 to 17 years of age and adult subjects [see Adverse Reactions (6.1) and Clinical Studies (14)].

Safety and effectiveness of ADBRY have not been established in pediatric patients younger than 12 years of age.

8.5 Geriatric Use

Of the 1605 subjects exposed to ADBRY in 5 atopic dermatitis trials in the initial treatment period of up to 16 weeks, 77 subjects were 65 years or older. Clinical studies did not include sufficient numbers of subjects aged 65 and over to determine whether they respond differently from younger subjects [see Clinical Pharmacology (12.3)].

10 OVERDOSAGE

There is no specific treatment for ADBRY overdose. In the event of overdosage, contact Poison Control (1-800-222-1222) for latest recommendations and monitor the patient for any signs or symptoms of adverse reactions and institute appropriate symptomatic treatment immediately.

11 DESCRIPTION

Tralokinumab-ldrm, an interleukin-13 antagonist, is a human IgG4 monoclonal antibody. Tralokinumab-ldrm is produced in mouse myeloma cells by recombinant DNA technology, consists of 1326 amino acids, and has a molecular weight of approximately 147 kilodaltons.

ADBRY (tralokinumab-ldrm) injection is a sterile, preservative-free, clear to opalescent, colorless to pale yellow solution for subcutaneous use supplied as either a single-dose prefilled syringe with needle guard in a siliconized Type-1 clear glass syringe or a single-dose autoinjector with a siliconized Type-1 clear glass syringe inside. None of the components of the prefilled syringe, autoinjector or the needle guard are made with natural rubber latex.

Each prefilled syringe delivers 150 mg tralokinumab-ldrm in 1 mL and the inactive ingredients: acetic acid (0.3 mg), polysorbate 80 (0.1 mg), sodium acetate trihydrate (6 mg), sodium chloride (5 mg), and Water for Injection, at an approximate pH of 5.5.

Each autoinjector delivers 300 mg tralokinumab-ldrm in 2 mL and the inactive ingredients: acetic acid (0.6 mg), polysorbate 80 (0.2 mg), sodium acetate trihydrate (12 mg), sodium chloride (10 mg), and Water for Injection, at an approximate pH of 5.5.

12 CLINICAL PHARMACOLOGY

12.1 Mechanism of Action

Tralokinumab-ldrm is a human IgG4 monoclonal antibody that specifically binds to human interleukin-13 (IL-13) and inhibits its interaction with the IL-13 receptor α1 and α2 subunits (IL-13Rα1 and IL-13Rα2). IL-13 is a naturally occurring cytokine of the Type 2 immune response. Tralokinumab-ldrm inhibits the bioactivity of IL-13 by blocking IL-13 interaction with IL-13Rα1/IL-4Rα receptor complex. Tralokinumab-ldrm inhibits IL-13-induced responses including the release of proinflammatory cytokines, chemokines and IgE.

12.2 Pharmacodynamics

ADBRY was associated with decreased concentrations of Th2 and Th22 immunity biomarkers in the blood, such as thymus and activation-regulated chemokine (TARC/CCL17), periostin, IL-22, lactate dehydrogenase (LDH) and serum IgE. ADBRY decreased expression of keratin 16 and Ki-67 in AD skin, and upregulated protein expression of loricrin. ADBRY suppressed expression of genes in the Th2 pathway, including CCL17, CCL18 and CCL26 as well as markers of Th17- and Th22-regulated genes in lesional skin. The clinical relevance of these is not fully understood.

Immune Response to Non-live Vaccines during Treatment

Immune responses to non-live vaccines were assessed in a trial in which adult subjects with atopic dermatitis were treated with an initial dose of 600 mg (four 150 mg injections) followed by 300 mg every other week administered as subcutaneous injection. After 12 weeks of ADBRY administration, subjects were vaccinated with a combined tetanus, diphtheria, and acellular pertussis vaccine, and a meningococcal vaccine. Antibody responses were assessed 4 weeks later. Antibody response to tetanus, diphtheria, acellular pertussis, and a meningococcal vaccine was similar in tralokinumab-ldrm treated and placebo treated subjects. Immune responses to other vaccines were not assessed.

12.3 Pharmacokinetics

In adults, the mean (SD) steady-state trough concentration of tralokinumab-ldrm ranged from 98.0 (41.1) mcg/mL to 101.4 (42.7) mcg/mL following administration of ADBRY at 300 mg every other week. Tralokinumab-ldrm exposure increased proportionally over a dosage range up to 2100 mg for a 70 kg subject (30 mg/kg IV) (3.5 times the maximum approved recommended dosage). Steady-state tralokinumab-ldrm concentrations were achieved by week 16 following a 600 mg starting dose and 300 mg every other week.

Absorption

The absolute bioavailability of tralokinumab-ldrm was estimated to be 76%. The time to maximum tralokinumab-ldrm concentrations (tmax) was 5 to 8 days after administration.

Distribution

The volume of distribution of tralokinumab-ldrm was estimated to be approximately 4.2 L.

Elimination

The half-life of tralokinumab-ldrm was 3 weeks and systemic clearance was estimated to be 0.149 L/day.

Metabolism

Tralokinumab-ldrm is expected to be metabolized into small peptides by catabolic pathways.

Specific Populations

Geriatric Patients, Patients with Renal and Hepatic Impairment

No clinically significant differences in the pharmacokinetics of tralokinumab-ldrm were observed based on age (ranged from 18 – 92 years), sex, mild to moderate renal impairment, or mild hepatic impairment. The effect of severe renal impairment or moderate to severe hepatic impairment on the pharmacokinetics of tralokinumab-ldrm is unknown.

Pediatric Patients

In subjects 12 to 17 years of age with atopic dermatitis, the mean (SD) steady-state trough concentration of tralokinumab-ldrm was 59.6 mcg/mL (19.4) and 112.8 mcg/mL (39.2) following administration of ADBRY at 150 mg and 300 mg every other week, respectively.

Body Weight

The exposure of tralokinumab-ldrm decreases with increasing body weight. After 300 mg dose every 4 weeks, the median tralokinumab-ldrm exposure (AUC) of subjects with body weight of above 100 kg is expected to be 1.46-fold lower than that of subjects weighing below 100 kg [see Dosage and Administration (2.2)].

Drug Interaction Studies

Cytochrome P450 Substrates

The effects of tralokinumab on the pharmacokinetics of midazolam (CYP3A4 substrate), warfarin (CYP2C9 substrate), omeprazole (CYP2C19 substrate), metoprolol (CYP2D6 substrate), and caffeine (CYP1A2 substrate) were evaluated in a clinical trial in 18-20 subjects with moderate to severe atopic dermatitis receiving an initial SC dose of 600 mg followed by 300 mg SC every other week for 14 weeks. No clinically significant changes in the exposure (AUC or Cmax) of the CYP450 substrates after multiple tralokinumab administrations were observed compared to that when administered alone.

12.6 Immunogenicity

The observed incidence of anti-drug antibodies is highly dependent on the sensitivity and specificity of the assay. Differences in assay methods preclude meaningful comparisons of the incidence of anti-drug antibodies in the trials described below with the incidence of anti-drug antibodies in other trials, including those of ADBRY or of other tralokinumab products.

In ECZTRA 1, ECZTRA 2, and ECZTRA 3, and the vaccine-response trial, the incidence of anti-drug antibodies (ADA) during the initial 16-week treatment period was 1.4% for subjects treated with ADBRY 300 mg every other week and in 1.3% for subjects treated with placebo; neutralizing antibodies were seen in 0.1% of subjects treated with ADBRY and 0.2% of subjects treated with placebo.

Across all trial periods, the ADA incidence for subjects who received ADBRY was 4.6%; 0.9% had persistent ADA and 1.0% had neutralizing antibodies.

No clinically significant differences in the pharmacokinetics, safety, or efficacy of tralokinumab-ldrm were observed in patients who tested positive for anti-tralokinumab-ldrm antibody (including neutralizing antibodies).

In the open-label long-term extension trial (ECZTEND), anti-drug-antibody (ADA) responses were assessed up to 248 weeks and were not associated with any impact on tralokinumab exposure or safety.

13 NONCLINICAL TOXICOLOGY

13.1 Carcinogenesis, Mutagenesis, Impairment of Fertility

Animal studies have not been conducted to evaluate the carcinogenic or mutagenic potential for tralokinumab-ldrm.

No effects on fertility parameters such as reproductive organs, menstrual cycle and sperm analysis were observed in male or female sexually mature cynomolgus monkeys that were subcutaneously administered tralokinumab-ldrm at doses up to 350 mg/animal (10 times the MRHD on a mg/kg basis of 10 mg/kg/week) in females once a week for three consecutive menstrual cycles (maximum of 15 doses) or 600 mg/animal (10 times the MRHD on a mg/kg basis of 10 mg/kg/week) in males once a week for 13 weeks. The monkeys were not mated to evaluate fertility.

14 CLINICAL STUDIES

Adults

The efficacy of ADBRY was assessed in three randomized, double-blind, placebo-controlled trials [ECZTRA 1 (NCT03131648), ECZTRA 2 (NCT03160885), and ECZTRA 3 (NCT03363854)]. Efficacy was assessed in a total of 1934 subjects 18 years of age and older with moderate-to-severe atopic dermatitis (AD) not adequately controlled by topical medication(s). Disease severity was defined by an Investigator's Global Assessment (IGA) score ≥ 3 in the overall assessment of AD lesions on a severity scale of 0 to 4, an Eczema Area and Severity Index (EASI) score ≥16 on a scale of 0 to 72, and a minimum body surface area (BSA) involvement of ≥10%. At baseline, 58% of subjects were male, 69% of subjects were White, 50% of subjects had a baseline IGA score of 3 (moderate AD), and 50% of subjects had a baseline IGA score of 4 (severe AD). The baseline mean EASI score was 32 and the baseline weekly averaged Worst Daily Pruritus Numeric Rating Scale (NRS) was 8 on a scale of 0-10.

In all three trials, subjects received subcutaneous injections of ADBRY 600 mg or placebo on Day 0, followed by 300 mg every other week or placebo for 16 weeks. Responders were defined as achieving an IGA 0 or 1 ("clear" or "almost clear") or EASI-75 (improvement of at least 75% in EASI score from baseline) at Week 16.

To evaluate maintenance of response in the monotherapy trials (ECZTRA 1 and ECZTRA 2), subjects responding to initial treatment with ADBRY 300 mg every other week were re-randomized to ADBRY 300 mg every other week, ADBRY 300 mg every 4 weeks or placebo every other week for another 36 weeks following first dose administration. Subjects randomized to placebo in the initial treatment period who achieved a clinical response at Week 16 continued to receive placebo every other week for another 36 weeks. Non-responders at Week 16, and subjects who lost clinical response during the maintenance period were placed on open-label treatment with ADBRY 300 mg every other week and optional use of TCS.

In the combination therapy trial (ECZTRA 3), subjects received either ADBRY 300 mg every other week with TCS or placebo with TCS and as needed topical calcineurin inhibitors (TCI) until Week 16. Subjects in the ADBRY 300 mg with TCS group who achieved clinical response at Week 16 were re-randomized to ADBRY 300 mg every other week with TCS or ADBRY every 4 weeks with TCS for another 16 weeks following first dose administration. Subjects in the placebo with TCS group who achieved clinical response at Week 16 continued on placebo with TCS for another 16 weeks. Subjects who did not achieve clinical response at Week 16 received ADBRY 300 mg every other week for another 16 weeks. A mid-potency TCS (i.e., mometasone furoate 0.1% cream) was dispensed at each dosing visit. Subjects were instructed to apply a thin film of the dispensed TCS as needed once daily to active lesions from Week 0 to Week 32 and were to discontinue treatment with TCS when control was achieved. An additional, lower potency TCS or TCI could be used at the investigator's discretion on areas of the body where use of the supplied TCS was not advisable, such as areas of thin skin.

All three trials assessed the primary endpoints of the proportion of subjects with an IGA 0 or 1 at Week 16 and the proportion of subjects with EASI-75 at Week 16. Secondary endpoints included the reduction of Worst Daily Pruritus NRS (weekly average) of at least 4 points on the 11-point itch NRS from baseline to Week 16.

Clinical Response at Week 16 (ECZTRA 1, ECZTRA 2, and ECZTRA 3)

The results of the ADBRY monotherapy trials (ECZTRA 1 and ECZTRA 2) and the ADBRY with TCS trial (ECZTRA 3) are presented in Table 2.

Table 2: Efficacy Results of ADBRY With or Without TCS at Week 16 (ECZTRA 1, ECZTRA 2, and ECZTRA 3) in Subjects with Moderate-to-Severe AD
 | ECZTRA 1 |  | ECZTRA 2 |  | ECZTRA 3
 | ADBRY 300 mg every other week | Placebo | ADBRY 300 mg every other week | Placebo | ADBRY 300 mg every other week + TCS | Placebo + TCS
Number of subjects randomized and dosed (FAS) [Full Analysis Set (FAS) includes all subjects randomized and dosed.] | 601 | 197 | 577 | 193 | 243 | 123
IGA 0 or 1 [Responders was defined as a subject with an IGA 0 or 1 ("clear" or "almost clear").] , [Subjects who received rescue treatment or with missing data were considered as non-responders.] | 16% | 7% | 21% | 9% | 38% | 27%
Difference from Placebo | 9% |  | 12% |  | 11%
(95% CI) | (4%, 13%) |  | (7%, 17%) |  | (1%, 21%)
EASI-75 | 25% | 13% | 33% | 10% | 56% | 37%
Difference from Placebo | 12% |  | 22% |  | 20%
(95% CI) | (6%, 18%) |  | (17%, 28%) |  | (9%, 30%)
Number of subjects with baseline Worst Daily Pruritus NRS (weekly average) score ≥4 | 594 | 194 | 563 | 192 | 240 | 123
Worst Daily Pruritus NRS (≥4 point reduction) | 20% | 10% | 25% | 9% | 46% | 35%
Difference from Placebo | 10% |  | 16% |  | 11%
(95% CI) | (4%, 15%) |  | (11%, 21%) |  | (1%, 22%)
Abbreviations: AD = Atopic Dermatitis CI = Confidence Interval.
Note: Difference and 95% CI are based on the CMH test stratified by region and baseline IGA score.

A higher proportion of subjects in the ADBRY 300 mg every other week arm achieved EASI-90 compared to placebo in the three pivotal trials.

Examination of age, gender, race, body weight, and previous treatment, including immunosuppressants, did not identify differences in response to ADBRY 300 mg every other week among these subgroups.

Monotherapy Trials (ECZTRA 1 and ECZTRA 2) – Maintenance Period (Week 16-52)

In ECZTRA 1, 179 ADBRY 300 mg every other week responders (IGA 0/1 or EASI-75) were re-randomized (and dosed) at Week 16 to ADBRY 300 mg every other week (68 subjects), ADBRY 300 mg every 4 weeks (76 subjects) or placebo (35 subjects). Among these subjects, 39 subjects in ADBRY 300 mg every other week arm, 36 subjects in ADBRY 300 mg every 4 weeks arm and 19 subjects in placebo arm were IGA 0/1 responders at Week 16. Maintenance of IGA 0/1 response at Week 52 was as follows: 20 subjects (51%) in every other week arm, 14 subjects (39%) in every 4 weeks arm and 9 subjects (47%) in the placebo arm. Among the re-randomized subjects, 47 subjects in ADBRY 300 mg every other week arm, 57 subjects in ADBRY 300 mg every 4 weeks arm and 30 subjects in placebo arm were EASI-75 responders at Week 16. Maintenance of EASI-75 response at Week 52 was as follows: 28 subjects (60%) in every other week arm, 28 subjects (49%) in every 4 weeks arm and 10 subjects (33%) in the placebo arm.

In ECZTRA 2, 218 ADBRY 300 mg every other week responders (IGA 0/1 or EASI-75) were re-randomized (and dosed) at Week 16 to ADBRY 300 mg every other week (90 subjects), ADBRY 300 mg every 4 weeks (84 subjects) or placebo (44 subjects). Among these subjects, 53 subjects in ADBRY 300 mg every other week arm, 44 subjects in ADBRY 300 mg every 4 weeks arm and 26 subjects in placebo arm were IGA 0/1 responders at Week 16. Maintenance of IGA 0/1 response at Week 52 was as follows: 32 subjects (60%) in every other week arm, 22 subjects (50%) in every 4 weeks arm and 6 subjects (23%) in the placebo arm. Among the re-randomized subjects, 76 subjects in ADBRY 300 mg every other week arm, 69 subjects in ADBRY 300 mg every 4 weeks arm and 40 subjects in placebo arm were EASI-75 responders at Week 16. Maintenance of EASI-75 response at Week 52 was as follows: 43 subjects (57%) in every other week arm, 38 subjects (55%) in every 4 weeks arm and 8 subjects (20%) in the placebo arm.

Concomitant TCS Trial (ECZTRA 3) – Maintenance Period (Week 16-32)

In ECZTRA 3, 131 ADBRY 300 mg every other week + TCS responders (IGA 0/1 or EASI-75) were re-randomized (and dosed) at Week 16 to ADBRY 300 mg every other week + TCS (65 subjects) or ADBRY 300 mg every 4 weeks + TCS (66 subjects). Among these subjects, 45 subjects in ADBRY 300 mg every other week + TCS arm and 46 subjects in ADBRY 300 mg every 4 weeks + TCS arm were IGA 0/1 responders at Week 16. Maintenance of IGA 0/1 response at Week 32 was as follows: 40 subjects (89%) in every other week arm and 35 subjects (76%) in every 4 weeks arm. Among the re-randomized subjects, 65 subjects in ADBRY 300 mg every other week arm and 62 subjects in ADBRY 300 mg every 4 weeks arm were EASI-75 responders at Week 16. Maintenance of EASI-75 response at Week 32 was as follows: 60 subjects (92%) in every other week arm and 56 subjects (90%) in every 4 weeks arm.

Pediatric Subjects 12 Years of Age and Older

The efficacy of ADBRY monotherapy in pediatric subjects 12 years of age and older was assessed in a multicenter, randomized, double-blind, placebo-controlled trial (ECZTRA 6; NCT03526861) in 289 subjects 12 to 17 years of age with moderate-to-severe AD defined by IGA score ≥ 3 in the overall assessment of AD lesions on a severity scale of 0 to 4, an EASI score ≥ 16 at baseline, and a minimum BSA involvement of ≥10%. Eligible subjects enrolled into this trial had previous inadequate response to topical medication.

A total of 98 subjects received an initial dose of ADBRY 300 mg followed by 150 mg every other week up to Week 16. Subjects who met the clinical response criteria (IGA of 0 or 1 or EASI-75) at Week 16 without the use of rescue medication were re-randomized in a 1:1 ratio to either ADBRY every other week or every 4 weeks up to Week 52, receiving the same dose as during the initial 16-week treatment period. Subjects who did not meet the clinical response criteria at Week 16 or did not maintain the response during the maintenance treatment period, or used rescue medication during the initial treatment period were transferred to open-label treatment with ADBRY 300 mg every other week with optional use of topical corticosteroids. Subjects randomized to placebo in the initial treatment period who achieved a clinical response at Week 16 continued to receive placebo every other week in the maintenance treatment period.

In this trial, the mean subject age was 14.6 years (range: 12 to 17 years), the mean weight was 61.5 kg, 48% of subjects were female, 57% were White, 25% were Asian, and 11% were Black. For ethnicity, 91.3% of subjects identified as non-Hispanic/Latino and 8.7% identified as Hispanic/Latino. At baseline, 53% of subjects had a baseline IGA score of 3 (moderate AD), 47% of subjects had a baseline IGA score of 4 (severe AD), the mean BSA involvement was 51%, and 21% of subjects had received prior systemic immunosuppressants (cyclosporine, methotrexate, azathioprine and mycophenolate). Also, at baseline the mean EASI score was 32, the baseline Adolescent Worst Pruritus NRS score was 8. Overall, 84% of subjects had at least one co-morbid allergic condition; 68% had allergic rhinitis, 51% had asthma, and 57% had food allergies.

The primary endpoints were the proportion of subjects with IGA 0 or 1 at Week 16 ("clear" or "almost clear") and the proportion of patients with EASI-75 (improvement of at least 75% in EASI from baseline) at Week 16. Secondary endpoints included the reduction in itch, as measured by the proportion of subjects with ≥4 point improvement in Adolescent Worst Pruritus NRS from baseline.

The efficacy results at Week 16 for subjects 12 to 17 years of age are presented in Table 3.

Table 3: Efficacy Results of ADBRY Monotherapy in Subjects 12 to 17 Years of Age at Week 16 in Subjects with Moderate-to-Severe AD (ECZTRA 6)
 | ADBRY 150 mg every other week | Placebo
Number of subjects randomized and dosed (FAS) [Full Analysis Set (FAS) includes all subjects randomized and dosed.] | 98 | 94
IGA 0 or 1 [Subjects who received rescue treatment from week 2 to week 16 or had missing data were considered non-responders.] , [Responder was defined as a subject with IGA 0 or 1 ("clear" or "almost clear" on a 0-4 IGA scale).] | 21% | 4%
Difference from Placebo | 18%
(95% CI) | (8%, 27%)
EASI-75 | 29% | 6%
Difference from Placebo | 23%
(95% CI) | (12%, 33%)
Number of subjects with baseline Worst Daily Pruritus NRS (weekly average) score ≥4 | 95 | 90
Worst Daily Pruritus NRS(≥4 point reduction) , [The percentage is calculated relative to the number of subjects with a baseline value ≥4.] | 23% | 3%
Difference from Placebo | 20%
(95% CI) | (11%, 29%)
Abbreviations: AD = Atopic Dermatitis, CI = Confidence Interval

In ECZTRA 6, a higher proportion of subjects in the ADBRY 150 mg every other week group achieved EASI-90 compared to placebo.

16 HOW SUPPLIED/STORAGE AND HANDLING

How Supplied

ADBRY (tralokinumab-ldrm) injection is a sterile, clear to opalescent, colorless to pale yellow solution, supplied in a single-dose prefilled syringe with a 27-gauge, ½ inch needle and a needle guard, or a single-dose autoinjector with a 27-gauge, ½ inch needle.

Each prefilled syringe delivers 150 mg of ADBRY in 1 mL solution (NDC 50222-346-01).

Each autoinjector delivers 300 mg of ADBRY in 2 mL solution (NDC 50222-350-00).

ADBRY is available in pack sizes containing either 2 or 4 prefilled syringes with needle guard or 1 or 2 autoinjectors.

150 mg in a 1 mL prefilled syringe – Pack Size | NDC #
Two cartons (multipack) containing 4 prefilled syringes | NDC 50222-346-04
One carton containing 2 prefilled syringes | NDC 50222-346-02

300 mg in a 2 mL autoinjector – Pack Size | NDC #
One carton containing 2 autoinjectors | NDC 50222-350-02
One carton containing 1 autoinjector | NDC 50222-350-01

Storage and Handling

ADBRY does not contain preservatives. Discard any unused portion.

Store refrigerated at 2°C to 8°C (36°F to 46°F) in the original carton to protect from light.

If necessary, ADBRY may be kept at room temperature up to 30°C (86°F) for a maximum of 14 days in the original carton. Do not store above 30°C (86°F). Do not put ADBRY back in the refrigerator after reaching room temperature. If the carton needs to be removed permanently from refrigerator, the date of removal may be recorded on the outer carton in the space provided. After removal from the refrigerator, ADBRY must be used within 14 days or discarded.

Do not expose ADBRY to heat or direct sunlight.

Do not freeze. Do not shake.

17 PATIENT COUNSELING INFORMATION

Advise the patients to read the FDA-approved patient labeling (Patient Information and Instructions for Use).

Administration Instructions

Instruct patients or caregivers:

- to perform the first self-injection under the supervision and guidance of a qualified healthcare provider for proper training in subcutaneous injection technique.
- to inject the full dose of ADBRY.
- to follow sharps disposal recommendations [see Instructions for Use].

Hypersensitivity

Advise patients to discontinue ADBRY and to seek immediate medical attention if they experience any symptoms of systemic hypersensitivity reactions [see Warnings and Precautions (5.1)].

Conjunctivitis and Keratitis

Advise patients to consult their healthcare provider if new onset or worsening eye symptoms develop [see Adverse Reactions (6.1)].

Risk of Infection with Live Vaccines

Instruct patients to inform the healthcare provider that they are taking ADBRY prior to a potential vaccination [see Warnings and Precautions (5.4)].

Pregnancy Registry

There is a pregnancy exposure registry that monitors pregnancy outcomes in women exposed to ADBRY during pregnancy. Encourage participation and advise patients about how they may enroll in the registry [see Use in Specific Populations (8.1)].

Manufactured by:
LEO Pharma A/S
Industriparken 55
Ballerup, Denmark DK-2750
U.S. License No. 2169

Distributed by:
LEO Pharma Inc.
Madison, NJ 07940, USA

ADBRY® is a registered trademark of LEO Pharma A/S.
© 2025 LEO Pharma Inc. All rights reserved.

PATIENT INFORMATION
ADBRY® [ad'-bree]
(tralokinumab-ldrm)
injection, for subcutaneous use

What is ADBRY?

- ADBRY is a prescription medicine used to treat people 12 years of age and older with moderate-to-severe atopic dermatitis (eczema) that is not well controlled with prescription therapies used on the skin (topical), or who cannot use topical therapies. ADBRY can be used with or without topical corticosteroids.
- It is not known if ADBRY is safe and effective in children under 12 years of age.

Do not use ADBRY if you are allergic to tralokinumab or to any of the ingredients in ADBRY. See the end of this leaflet for a complete list of ingredients in ADBRY.

Before using ADBRY, tell your healthcare provider about all your medical conditions, including if you:

- have eye problems.
- have a parasitic (helminth) infection.
- are scheduled to receive any vaccinations.
- are pregnant or plan to become pregnant. It is not known whether ADBRY will harm your unborn baby.
  Pregnancy Exposure Registry: There is a pregnancy exposure registry for women who use ADBRY during pregnancy. The purpose of this registry is to collect information about the health of you and your baby. You or your healthcare provider can get information and enroll you in this registry by calling 1-877-311-8972 or visiting https://mothertobaby.org/ongoing-study/adbry-tralokinumab/.
- are breastfeeding or plan to breastfeed. It is not known whether ADBRY passes into your breast milk and if it can harm your baby.

Tell your healthcare provider about all of the medicines you take, including prescription and over-the-counter medicines, vitamins, and herbal supplements.

How should I use ADBRY?

- See the detailed "Instructions for Use" that comes with ADBRY for information on how to prepare and inject ADBRY and how to properly store and throw away (dispose of) used ADBRY prefilled syringes and autoinjectors.
- Use ADBRY exactly as prescribed by your healthcare provider.
- Your healthcare provider will tell you how much ADBRY to inject and when to inject it.
- ADBRY comes as a single-dose prefilled syringe with needle guard or as an autoinjector.
- ADBRY is given as an injection under the skin (subcutaneous injection).
- If your healthcare provider decides that you or a caregiver can give the injections of ADBRY, you or your caregiver should receive training on the right way to prepare and inject ADBRY. Do not try to inject ADBRY until you have been shown the right way by your healthcare provider. In children 12 years of age and older, it is recommended that ADBRY be given by or under supervision of an adult.
- If you miss a dose, inject the missed dose as soon as possible, then continue with your next dose at your regular scheduled time.
- If you inject too much ADBRY, call your healthcare provider or Poison Help line at 1-800-222-1222 or go to the nearest hospital emergency room right away.
- Your healthcare provider may prescribe other medicines to use with ADBRY. Use the other prescribed medicines exactly as your healthcare provider tells you to.

What are the possible side effects of ADBRY?
ADBRY can cause serious side effects, including:

- Allergic reactions (hypersensitivity), including a severe reaction known as anaphylaxis. Stop using ADBRY and tell your healthcare provider or get emergency help right away if you get any of the following symptoms:

- breathing problems
- swelling of the face, mouth, and tongue
- hives
- itching

- fainting, dizziness, feeling lightheaded (low blood pressure)
- skin rash

- Eye problems. Tell your healthcare provider if you have any new or worsening eye problems, including eye pain or changes in vision.

The most common side effects of ADBRY include:

- upper respiratory tract infections
- eye and eyelid inflammation, including redness, swelling, and itching
- injection site reactions
- high count of a certain white blood cell (eosinophilia)

These are not all of the possible side effects of ADBRY.
Call your doctor for medical advice about side effects. You may report side effects to FDA at 1-800-FDA-1088.

How should I store ADBRY?

- Store ADBRY in a refrigerator between 36°F to 46°F (2°C to 8°C).
- Store ADBRY in the original carton and protect from light until you are ready to use them.
- ADBRY can be stored in the original carton at room temperature up to 86°F (30°C) for up to 14 days. If removed from the refrigerator, write down the date of removal on the back of the carton, and use ADBRY within 14 days. Throw away (dispose of) ADBRY in a sharps disposal container if left out of the refrigerator for more than 14 days.
- Do not freeze ADBRY. Do not use if they have been frozen.
- Do not shake ADBRY.
- Do not heat ADBRY.
- Do not put ADBRY into direct sunlight.

Keep ADBRY and all medicines out of the reach of children.

General information about the safe and effective use of ADBRY.
Medicines are sometimes prescribed for purposes other than those listed in a Patient Information leaflet. Do not use ADBRY for a condition for which it was not prescribed. Do not give ADBRY to other people, even if they have the same symptoms you have. It may harm them. You can ask your pharmacist or healthcare provider for information about ADBRY that is written for health professionals.

What are the ingredients in ADBRY?
Active ingredient: tralokinumab-ldrm
Inactive ingredients: acetic acid, polysorbate 80, sodium acetate trihydrate, sodium chloride, and water for injection.
Manufactured by: LEO Pharma A/S Industriparken 55, DK-2750 Ballerup, Denmark
Distributed by: LEO Pharma Inc., Madison, NJ 07940, USA
U.S. License No. 2169
ADBRY® is a registered trademark of LEO Pharma A/S.
© 2025 LEO Pharma Inc. All rights reserved.
For more information about ADBRY, go to www.ADBRY.com or call 1-844-MY-ADBRY (1-844-692-3279).

This Patient Information has been approved by the U.S. Food and Drug Administration.

Issued: 12/2025

INSTRUCTIONS FOR USE

ADBRY® [ad'-bree]
(tralokinumab-ldrm)
injection, for subcutaneous use

This Instructions for Use contains information on how to inject ADBRY.

Read this Instructions for Use before you start using the ADBRY prefilled syringe and each time you get a refill. There may be new information. This information does not take the place of talking to your healthcare provider about your medical condition or your treatment.

Keep this Instructions for Use and refer to it as needed.

Each single-dose prefilled syringe contains 150 mg of ADBRY. The ADBRY prefilled syringes are for one time use only.

Important Information You Need to Know Before Injecting ADBRY:

- Your healthcare provider should show you or your caregiver how to prepare and inject a dose of ADBRY using the prefilled syringe before you inject ADBRY for the first time. Talk to your healthcare provider if you have any questions about how to inject ADBRY the right way.
- ADBRY is given as an injection under the skin (subcutaneous injection).
- Do not inject yourself or someone else until you have been shown how to inject ADBRY the right way.
- In children 12 years of age and older, it is recommended that ADBRY be given by or under supervision of an adult.
- Talk to your healthcare provider about your prescribed dose before injecting ADBRY.
- Rotate the injection site each time you give an injection.
- The ADBRY prefilled syringe has a needle guard that will be activated to cover the needle after the injection is finished.
- Do not remove the needle cover until just before you give the injection.
- Do not share or reuse your ADBRY prefilled syringe.
- Do not inject through clothes.

Storing ADBRY

- Store ADBRY prefilled syringes in a refrigerator between 36°F to 46°F (2°C to 8°C).
- Store ADBRY prefilled syringes in the original carton to protect from light until you are ready to use them.
- ADBRY can be stored in the original carton at room temperature up to 86°F (30°C) for up to 14 days.
- If left out of the refrigerator for more than 14 days, throw away (dispose of) the ADBRY prefilled syringes.

- Do not freeze ADBRY prefilled syringes.
  Do not use if they have been frozen.
- Do not shake the ADBRY prefilled syringes.
- Do not heat the ADBRY prefilled syringes.
- Do not put the ADBRY prefilled syringes into direct sunlight.
- Keep ADBRY prefilled syringes and all medicines out of the reach of children.

ADBRY prefilled syringe parts (see Figure A):

Figure A

Step 1: Setting up ADBRY injection

Figure B

1a: Gather the supplies needed for your injection. For each ADBRY dose you will need (see Figure B):

- A clean, flat, well-lit work surface, like a table
- Prescribed number of ADBRY prefilled syringe(s)
- An alcohol swab (not included in the carton)
- Clean cotton balls or gauze pads (not included in the carton)
- A puncture-resistant sharps disposal container (not included in the carton). See Step 5 "Disposing of ADBRY" at the end of this Instructions for Use.

Figure C

1b: Take the ADBRY prefilled syringe carton out of the refrigerator

- Check the expiration date (EXP) on the carton (see Figure C). Do not use if the expiration date on the carton has passed.
- When using the first prefilled syringe, check to make sure the seal on the ADBRY carton is intact.
- Do not use the ADBRY prefilled syringes if the seal on the carton is broken.

Figure D

1c: Determine how many ADBRY prefilled syringes you need for your dose

If you have been prescribed a 300 mg dose, you will need 2 syringes.

If you have been prescribed a 150 mg dose, you will only need 1 syringe and the remaining syringe should be returned to the refrigerator in its carton.

- Remove the ADBRY prefilled syringe(s) by grasping the body (not the plunger rod) of the ADBRY prefilled syringe (see Figure D).
- Do not touch the needle guard clips to keep from activating the safety device (needle guard) too soon.
- Do not remove the needle cover on the prefilled syringe until you have reached Step 3 and are ready to inject.

Figure E

1d: Let the ADBRY prefilled syringe(s) warm up to room temperature (see Figure E)

Place the ADBRY prefilled syringe(s) on the flat surface and wait 30 minutes before you inject ADBRY to let the prefilled syringe(s) warm up to room temperature 68°F to 86°F (20°C to 30°C). This will help to reduce discomfort.

- Do not microwave the prefilled syringes, run hot water over them, or leave them in direct sunlight.
- Do not shake the syringes.
- Do not remove the needle cover on the prefilled syringes until you have reached Step 3 and are ready to inject.
- Do not put the syringes back in the refrigerator after they have reached room temperature.

Figure F

1e: Inspect the ADBRY prefilled syringe(s) (see Figure F)

- Make sure ADBRY appears on the label.
- Check the expiration date printed on the syringe.
- Check the medicine through the viewing window. The medicine inside should be clear to slightly pearly and colorless to pale yellow.
- Do not use the ADBRY prefilled syringe, throw away and get a new one if:
  - the expiration date printed on the syringe has passed
  - the medicine is cloudy, discolored, or has particles in it
  - looks damaged or has been dropped
- You may see small air bubbles in the liquid. This is normal. You do not need to do anything about it.

Step 2: Choosing and preparing injection area

Figure G

2a: Choose the area for your injection (see Figure G)

- You may inject into your thighs or your stomach area (abdomen), but not within 2 inches (5 cm) of your belly button (navel).
- The upper arm can also be used if a caregiver gives the injection.
- Inject your dose into a different body area each time you inject ADBRY.
- If you need more than 1 injection for your dose, inject into the same body area, but at least 1 inch (3 cm) apart from each other.
- Do not inject where the skin is tender, damaged, bruised or scarred.

Figure H

2b: Wash your hands and prepare your skin

- Wash your hands with soap and water.
- Clean the injection area with an alcohol swab using a circular motion (see Figure H).
  - Let the area dry completely.
  - Do not blow or touch the cleaned area before injecting.

Step 3: Injecting ADBRY

Figure I

3a: Pull off the ADBRY needle cover

Hold the ADBRY prefilled syringe body with one hand, pull the needle cover straight off with your other hand (see Figure I) and throw it away in the sharps container.

- Do not try to recap the ADBRY prefilled syringe.
- Do not hold the plunger rod or plunger head while removing the needle cover.
- You may see a drop of liquid at the end of the needle. This is normal.
- Do not touch the needle, or let it touch any surface. If either of these occur, throw away the syringe and get a new one.

Figure J

3b: Insert the needle

With one hand, gently pinch and hold a fold of skin where you cleaned the injection area. With the other hand, insert the needle completely at about a 45-degree angle into your skin (see Figure J).

Figure K

3c: Inject the medicine

Use your thumb to firmly push down the plunger head all the way down (see Figure K). All the medicine is injected when you cannot push the plunger head any further.

Figure L

3d: Release and remove

Lift your thumb off the plunger head. The needle will automatically move back inside the syringe body and lock into place (see Figure L).

- Place a dry cotton ball or gauze pad over the injection site for a few seconds. Do not rub the injection site. If needed, cover the injection site with a small bandage.
- There may be a small amount of blood or liquid where you injected. This is normal.

Throw away the used ADBRY prefilled syringe in the sharps disposal container. See Step 5 "Disposing of ADBRY".

Step 4: Repeating for multiple injections

Figure M

If you need to give multiple injections for your prescribed dose, repeat step 3. The other injection(s) should be given into the same body area, but at least 1 inch (3 cm) away from each other.

Step 5: Disposing of ADBRY syringe(s)

Figure N

- Put the used ADBRY prefilled syringe(s) in an FDA-cleared sharps disposal container right away after use (see Figure N). Do not throw away the ADBRY prefilled syringe(s) in your household trash.
- If you do not have an FDA-cleared sharps disposal container, you may use a household container that is:
  - made of heavy-duty plastic,
  - can be closed with a tight-fitting, puncture-resistant lid, without sharps being able to come out,
  - upright and stable during use,
  - leak-resistant, and
  - properly labeled to warn of hazardous waste inside the container.
- When your sharps disposal container is almost full, you will need to follow your community guidelines for the right way to dispose of your sharps disposal container. There may be state or local laws about how you should throw away used needles and syringes. For more information about safe sharps disposal, and for specific information about sharps disposal in the state that you live in, go to the FDA's website at: http://www.fda.gov/safesharpsdisposal.
- Do not recycle your used sharps disposal container.

For more information go to www.ADBRY.com or call 1-844-692-3279. If you still have questions, call your healthcare provider.

Manufactured by: LEO Pharma A/S Industriparken 55, DK-2750 Ballerup, Denmark
Distributed by: LEO Pharma Inc., Madison, NJ 07940, USA
U.S. License No. 2169
ADBRY® is a registered trademark of LEO Pharma A/S.
© 2023 LEO Pharma Inc. All rights reserved.

This Instructions for Use has been approved by the U.S. Food and Drug Administration.

Revised 12/2023

INSTRUCTIONS FOR USE

ADBRY® [ad'-bree]
(tralokinumab-ldrm)
injection, for subcutaneous use
Single-Dose Autoinjector (300 mg/2 mL)

This Instructions for Use contains information on how to inject ADBRY.

Read this Instructions for Use before you start using the ADBRY Autoinjector and each time you get a refill. There may be new information. This information does not take the place of talking to your healthcare provider about your medical condition or your treatment.

Keep this Instructions for Use and refer to it as needed.

Each autoinjector contains 300 mg of ADBRY.
The ADBRY Autoinjector is for one-time use only.

Important Information You Need to Know Before Injecting ADBRY:

- ADBRY is given as an injection under the skin (subcutaneous injection).
- Your healthcare provider should show you how to prepare and inject ADBRY using the Autoinjector before you inject ADBRY for the first time. Talk to your healthcare provider if you have any questions about how to inject ADBRY the right way.
- Do not inject yourself or someone else until you have been shown how to inject ADBRY the right way.
- The ADBRY Autoinjector is for use in adults only.
- Talk to your healthcare provider about your prescribed dose before injecting ADBRY.
- For your initial dose, you will use 2 Autoinjectors. After the initial dose, you will use 1 Autoinjector for further doses.
- Rotate the injection area with each new injection.
- The ADBRY Autoinjector has a needle guard that will be activated to cover the needle after the injection is finished.
- Do not remove the cap until just before you give the injection.
- Do not share or reuse your ADBRY Autoinjector.
- Do not inject through clothes.

ADBRY Autoinjector parts (see Figure A):

Figure A

Storing ADBRY

- Store ADBRY Autoinjectors in a refrigerator between 36°F to 46°F (2°C to 8°C).
- Store ADBRY Autoinjectors in the original carton and protect from light until you are ready to use them.
- ADBRY can be stored in the original carton at room temperature up to 86°F (30°C) for up to 14 days. If removed from the refrigerator, write down the date of removal on the back of the carton, and use the autoinjector within 14 days. Throw away (dispose of) the autoinjectors in a sharps disposal container if left out of the refrigerator for more than 14 days.
- Do not freeze ADBRY Autoinjectors. Do not use if they have been frozen.
- Do not shake ADBRY.
- Do not heat ADBRY.
- Do not put ADBRY into direct sunlight.
- Keep ADBRY Autoinjectors and all medicines out of the reach of children. Contains small parts.

Step 1: Setting up ADBRY injection

Figure B

1a: Gather the supplies needed for your injection.
For each ADBRY dose you will need (see Figure B):

- A clean, flat, well-lit work surface, like a table
- 1 ADBRY Autoinjector
- An alcohol swab (not included in the carton)
- Clean cotton balls or gauze pads (not included in the carton)
- A puncture-resistant sharps disposal container (not included in the carton)
  See Step 4 "Throwing away (Disposing of) ADBRY Autoinjectors" at the end of this Instructions for Use.

1b: Take the ADBRY Autoinjector carton out of the refrigerator

Figure C

Check the expiration date (EXP) on the carton (see Figure C).
Do not use if the expiration date on the carton has passed.

Check to make sure the seal on the carton is intact. Do not use the ADBRY Autoinjectors if the seal on the carton is broken.

1c: Remove the ADBRY Autoinjector from the carton

Figure D

Remove 1 autoinjector from the carton (see Figure D).

- When using the first autoinjector, put the carton with the remaining autoinjector back in the refrigerator.
- Do not remove the cap on the autoinjector until you have reached Step 3 and are ready to inject.

1d: Let the ADBRY Autoinjector warm up to room temperature

Figure E

Place the autoinjector on the flat surface and wait at least 45 minutes before you inject ADBRY to let the autoinjector warm up to room temperature 68°F to 86°F (20°C to 30°C) (see Figure E). This will help to reduce discomfort.

- Do not microwave the autoinjector, run hot water over it, or leave it in direct sunlight.
- Do not shake the autoinjector.
- Do not put the autoinjector back in the refrigerator after it has reached room temperature.

1e: Inspect the ADBRY Autoinjector (see Figure F)

Figure F

- Make sure ADBRY appears on the label.
- Check the expiration date (EXP) printed on the autoinjector label.
- Check the medicine through the viewing window. The medicine inside should be clear to slightly pearly and colorless to pale yellow.
- You may see small air bubbles in the liquid. This is normal. You do not need to do anything about it.

Do not use the ADBRY Autoinjector, throw away in a sharps disposal container and get a new one if:

- the expiration date printed on the autoinjector label has passed.
- the medicine is cloudy, discolored, or has particles in it.
- it looks damaged or has been dropped.

Step 2: Choosing and preparing injection area
2a: Choose the area for your injection (see Figure G)

Figure G

- You may inject into:
  - your stomach area (abdomen)
  - your thighs
  - your upper arm. To inject into your upper arm, you will need a caregiver to give you the injection.
- Do not inject within 2 inches (5 cm) of your belly button (navel).
- Rotate the body area with each injection. Do not use the same body area 2 times in a row.
- Do not inject where the skin is tender, damaged, bruised or scarred.

2b: Wash your hands and prepare your skin

Figure H

- Wash your hands with soap and water.
- Clean the injection area with an alcohol swab using a circular motion (see Figure H).
  - Let the area dry completely.
  - Do not blow or touch the cleaned area before injecting.

Step 3: Injecting ADBRY
3a: Pull off the ADBRY cap

Figure I

Hold the autoinjector with one hand, pull the cap straight off with your other hand (see Figure I) and throw it away in the sharps container. The needle guard is now exposed. It is there to prevent you from touching the needle.

- Do not try to recap the autoinjector. This could cause the injection to happen too soon or damage the needle.
- Do not try to touch or push on the needle guard with your finger. This could cause needle stick injury.

3b: Place the ADBRY Autoinjector at the injection area as shown in Figure J so that you can see the viewing window

Figure J

You can gently pinch the skin where you cleaned the injection area or give the injection without pinching the skin. Follow your healthcare provider´s instructions on how to inject.

- Place the needle guard of the autoinjector flat against your skin (90-degree angle) at the injection area you have cleaned. Make sure you can see the viewing window (see Figure J).
- Do not change the position of the autoinjector after the injection has started.

If the autoinjector is removed too soon, you may see a stream of medicine coming from the autoinjector. If this happens you may not have received your full dose. Call your healthcare provider.

3c: Press down on the ADBRY Autoinjector and hold pressure

Figure K

Press the autoinjector down firmly and hold it in place (see Figure K). You will hear a "click" to let you know that the injection has started and the yellow plunger will start to move.

The yellow plunger will move to the bottom of the viewing window as the medicine is being injected.
It may take up to 15 seconds to inject the full dose.

You will hear a second "click" when the yellow plunger fills the viewing window.

Keep pressing.

3d: Continue to press down for another 5 seconds

Figure L

After the second "click", continue to press the autoinjector firmly against your skin for 5 seconds to make sure you get your full dose (see Figure L).

3e: Remove the ADBRY Autoinjector

Figure M

Pull the autoinjector straight away from the injection area (see Figure M). The needle guard will slide down and lock into place over the needle.

Place a dry cotton ball or gauze pad over the injection area for a few seconds.
Do not rub the injection area.

There may be a small amount of blood or liquid where you injected. This is normal. If needed, cover the injection area with a small bandage.

3f: Check the viewing window

Figure N

Check the viewing window to make sure all the liquid has been injected (see Figure N).

If the yellow plunger does not fill the viewing window you may not have received the full dose. If this happens or if you have any other concerns, call your healthcare provider and call LEO Pharma at 877-494-4536 to report a product quality complaint.

Step 4: Throwing away (Disposing of) ADBRY Autoinjectors

Figure O

Put the used ADBRY Autoinjectors in an FDA-cleared sharps disposal container right away after use (see Figure O).

- Do not throw away the ADBRY Autoinjectors in your household trash.
- If you do not have an FDA-cleared sharps disposal container, you may use a household container that is:
  - made of a heavy-duty plastic,
  - can be closed with a tight-fitting, puncture-resistant lid, without sharps being able to come out,
  - upright and stable during use,
  - leak-resistant, and
  - properly labeled to warn of hazardous waste inside the container.
- When your sharps disposal container is almost full, you will need to follow your community guidelines for the right way to dispose of your sharps disposal container. There may be state or local laws about how you should throw away used ADBRY Autoinjectors. For more information about safe sharps disposal, and for specific information about sharps disposal in the state that you live in, go to the FDA's website at: http://www.fda.gov/safesharpsdisposal.
- Do not dispose of your used sharps disposal container in your household trash unless your community guidelines permit this. Do not recycle your used sharps disposal container.

For more information go to www.ADBRY.com or call 1-844-692-3279. If you still have questions, call your healthcare provider.

Manufactured by: LEO Pharma A/S Industriparken 55, DK-2750 Ballerup, Denmark
Distributed by: LEO Pharma Inc., Madison, NJ 07940, USA
U.S. License No. 2169

ADBRY® is a registered trademark of LEO Pharma A/S.
© 2024 LEO Pharma Inc. All rights reserved.

This Instructions for Use has been approved by the U.S. Food and Drug Administration.

Issued: June 2024

PRINCIPAL DISPLAY PANEL - 150 mg/mL Syringe Carton - NDC 50222-346-02

Adbry®
(tralokinumab-ldrm)
Injection
150 mg/mL per syringe

NDC 50222-346-02
Rx only

x 2

For Subcutaneous Use Only

One 1-mL single-dose prefilled syringe equals 150 mg
Two 1-mL single-dose prefilled syringes equal 300 mg

Carton contains:

- Two 1-mL single-dose prefilled syringes with needle guard
- Prescribing Information
- Instructions for Use and Patient Information

Store refrigerated at 36°F to 46°F (2°C to 8°C) in
the original carton to protect from light.

LEO®

PRINCIPAL DISPLAY PANEL - 150 mg/mL Syringe Carton - NDC 50222-346-04

Adbry®
(tralokinumab-ldrm)
Injection
150 mg/mL per syringe

NDC 50222-346-04
Rx only

x 4

For Subcutaneous Use Only

One 1-mL single-dose prefilled syringe equals 150 mg
Two 1-mL single-dose prefilled syringes equal 300 mg
Four 1-mL single-dose prefilled syringes equal 600 mg

Multipack contains:

- Two cartons
- Each carton contains two 1-mL single-dose prefilled syringes
  with needle guard which equal 300 mg

Store refrigerated at 36°F to 46°F (2°C to 8°C) in
the original carton to protect from light.

LEO®

PRINCIPAL DISPLAY PANEL - 300 mg/2 mL Autoinjector Carton - NDC 50222-350-01

Adbry®
(tralokinumab-ldrm)
Injection
300 mg/2 mL Single-dose Autoinjector

NDC 50222-350-01
Rx only

For Subcutaneous Use Only

One 2 mL Single-dose Autoinjector equals one dose of 300 mg

Carton contains:

- One Single-dose Autoinjector
- Prescribing Information
- Instructions for Use and Patient Information

Store refrigerated at 36°F to 46°F (2°C to 8°C) in
the original carton to protect from light.

LEO®

PRINCIPAL DISPLAY PANEL - 300 mg/2 mL Autoinjector Carton - NDC 50222-350-02

Adbry®
(tralokinumab-ldrm)
Injection
300 mg/2 mL Single-dose Autoinjector

NDC 50222-350-02
Rx only

x 2

For Subcutaneous Use Only

One 2 mL Single-dose Autoinjector equals one dose of 300 mg

Carton contains:

- Two Single-dose Autoinjectors
- Prescribing Information
- Instructions for Use and Patient Information

Store refrigerated at 36°F to 46°F (2°C to 8°C) in
the original carton to protect from light.
Dispense in this sealed carton.

LEO®